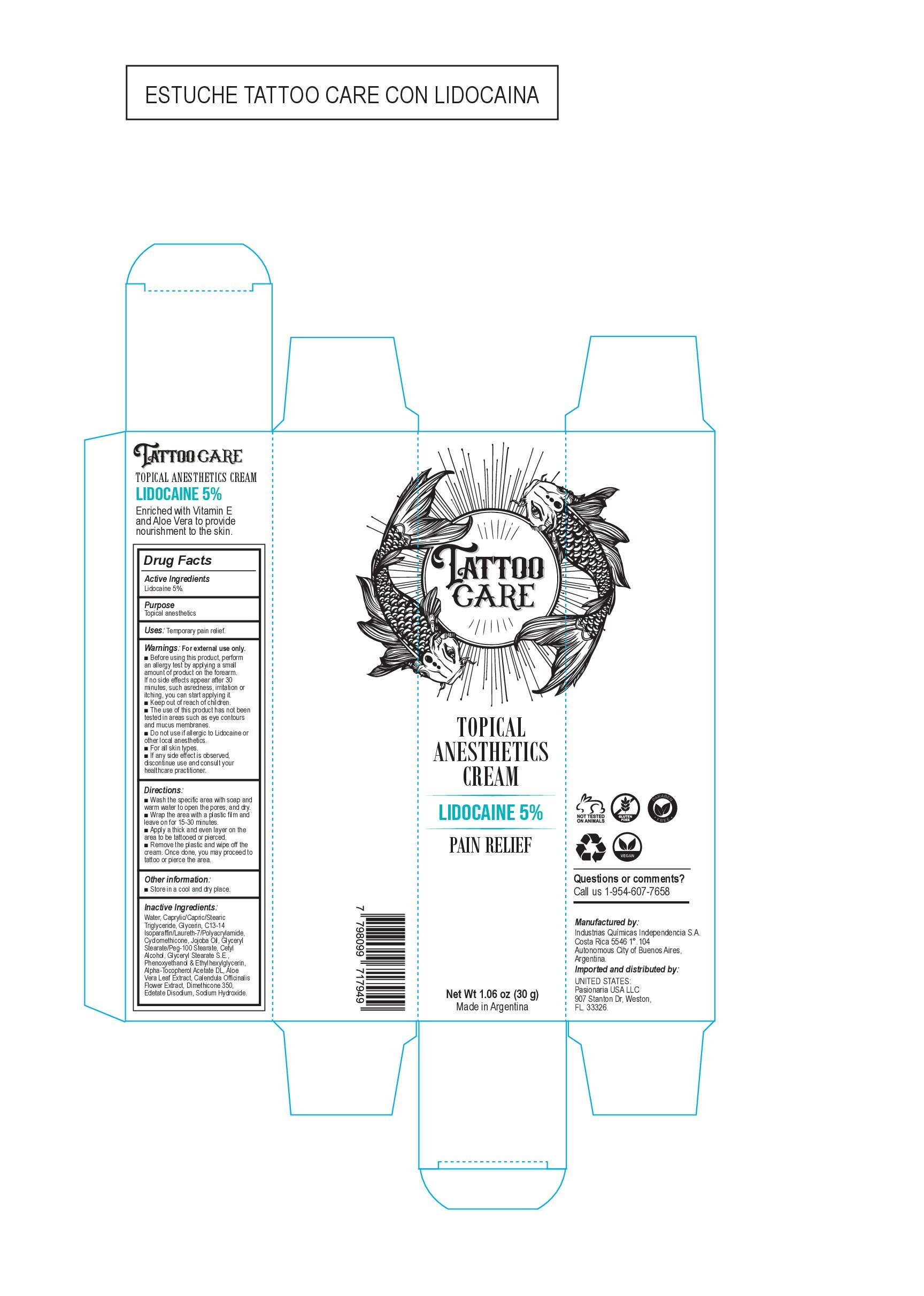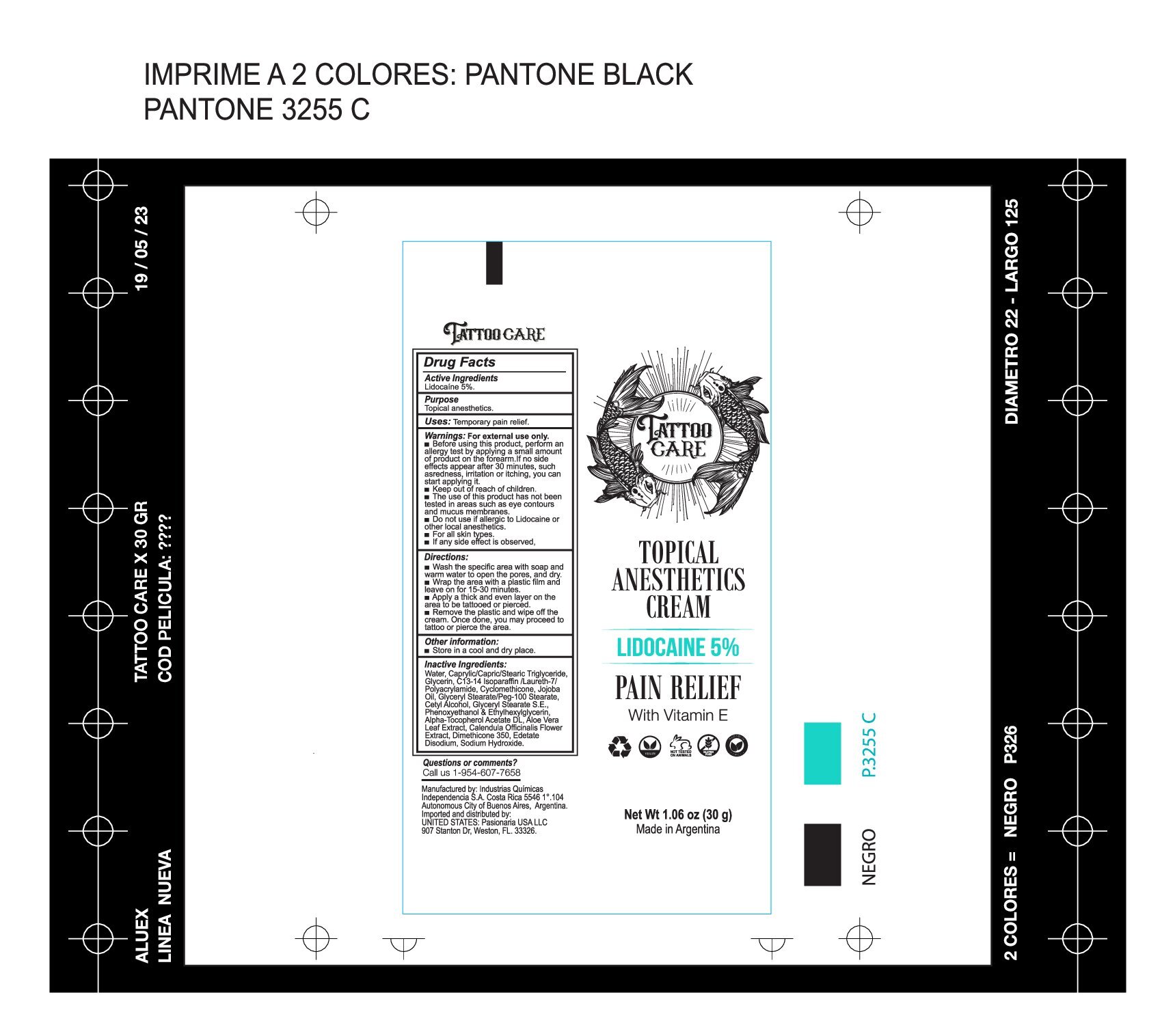 DRUG LABEL: TATOO CARE
NDC: 83527-1001 | Form: CREAM
Manufacturer: INDUSTRIAS QUIMICAS INDEPENDENCIA SA
Category: otc | Type: HUMAN OTC DRUG LABEL
Date: 20230616

ACTIVE INGREDIENTS: LIDOCAINE 5 g/100 g
INACTIVE INGREDIENTS: WATER; LAURETH-7; POLYACRYLAMIDE (10000 MW); CYCLOMETHICONE; JOJOBA OIL; GLYCERYL STEARATE SE; EDETATE DISODIUM; ETHYLHEXYLGLYCERIN; .ALPHA.-TOCOPHEROL ACETATE, DL-; ALOE VERA LEAF; CALENDULA OFFICINALIS FLOWER; SODIUM HYDROXIDE; CETYL ALCOHOL; PHENOXYETHANOL; DIMETHICONE 350; C13-14 ISOPARAFFIN; CAPRYLIC/CAPRIC/PALMITIC/STEARIC TRIGLYCERIDE; GLYCERIN; GLYCERYL STEARATE/PEG-100 STEARATE

Package label

Active ingredients

Lidocaine 5%

Ask your doctor

If any side effect is observed, discontinue use and consult your healthcare practicioner

Do not use if allergic to Lidocaine or other local anesthetics

Keep out of the reach of children

Pregnancy or Breast feeding

Do not use if you are pregnant or breast feeding

Purpose

Topical anesthethics

Questions or comments

Call us 1-954-607-7658

Warnings

If any side effect is observed, discontinued use and consult your healthcare practicioner

Directions

Wash the specific area with soap and warm water to open pores and dry. Apply a thick and even layer of the product

Dosage and administration

Apply a thick and even layer on the area

Warnings

For external use only.

- Before using this product perform an allergy test by applying a small amount of product on the forearm. If no side effect appear after 30 minutes, such asredness, irritation or itching, you can start applying it.
- Keep out of the reaching of children
- The use of this product has not been tested in areas such as eyes contours and mucus membranes.
- Do not use if allergic to lidocaine or other local anesthetics
- For all kind of skin
- If any side effect is observed, discontinue use and consult your healthcare practicioner

Inactive ingredients

WATER, CAPRYLIC/CAPRIC/STEARIC TRIGLYCERIDE, GLYCERIN, C13-14 ISOPARAFFIN/LAURETH-7/POLYACRYLAMIDE, CYCLOMETHICONE, JOJOBA OIL, GLYCERYL STEARATE /PEG-100 STEARATE, CETYL ALCOHOL, GLYCERYL STEARATE SE, PHENOXYETHANOL & ETHYLHEXYLGLYCERIN, ALPHA TOCOPHEROL ACETATE, DL ALOE VERA LEAF EXTRACT, CALENDULA OFFICINALIS FLOWER EXTRACT, DIMETHICONE 350, EDETATE DISODIUM, SODIUM HYDROXIDE

Indications

Temporary pain relief